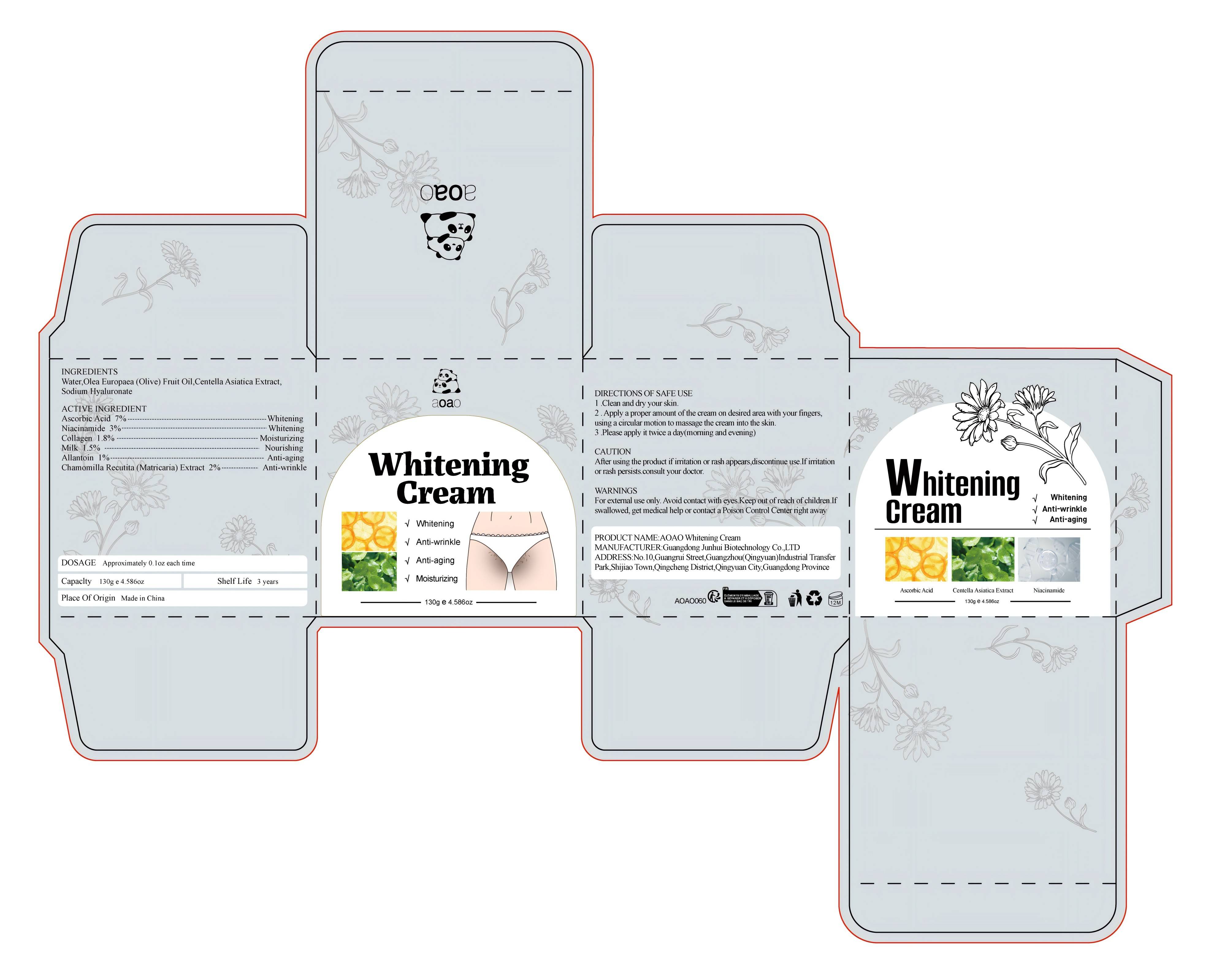 DRUG LABEL: AOAO Whitening Cream
NDC: 84509-023 | Form: CREAM
Manufacturer: Guangdong Junhui Biotechnology Co., LTD
Category: otc | Type: HUMAN OTC DRUG LABEL
Date: 20241013

ACTIVE INGREDIENTS: ALLANTOIN 1300 mg/130 g; NIACINAMIDE 3900 mg/130 g; MATRICARIA CHAMOMILLA WHOLE 2600 mg/130 g; COW MILK 1950 mg/130 g; COLLAGEN ALPHA-1(II) CHAIN 2340 mg/130 g; ASCORBIC ACID 9100 mg/130 g
INACTIVE INGREDIENTS: HYALURONATE SODIUM; OLIVE OIL; WATER; CENTELLA ASIATICA TRITERPENOIDS

Active Ingredients

Ascorbic Acid 7%
Niacinamide 3%
Chamomilla Recutita (Matricaria) Extract 2%
Collagen 1.80%
Milk 1.50%
Allantoin 1%

Purpose

Whitening
Anti-wrinkle
Moisturizing
Nourishing
Anti-aging

Uses

1 .Clean and dry your skin.
2 . Apply a proper amount of the cream on desired area with your fingers, using a circular motion to massage the cream into the skin.
3 .Please apply it twice a day(morning and evening)

Warnings

For external use only. Keep out ofreach of children.Avoid contact with eyes.

Keep out of reach of children. If swallowed, get medical help or contact a Poison Control Center right away

CAUTION

After using the product if irritation or rash appears,discontinue use.If irritation or
rash persists.consult your doctor.

DOSAGE

Approximately 0.1oz each time

Inactive Ingredients

Water,Olea Europaea (Olive) Fruit Oil,Centella Asiatica Extract,Sodium Hyaluronate

Product Name

AOAO Whitening Cream

Manufacturer

Guangdong Junhui Biotechnology Co., LTD

ADDRESS

No. 10, Guangrui Street, Guangzhou (Qingyuan) Industrial Transfer Park, Shijiao Town, Qingcheng District, Qingyuan City, Guangdong Province

Capacity

130g e 4.586 oz

Shelf Life

3 Years

Place of Origin

Made in China